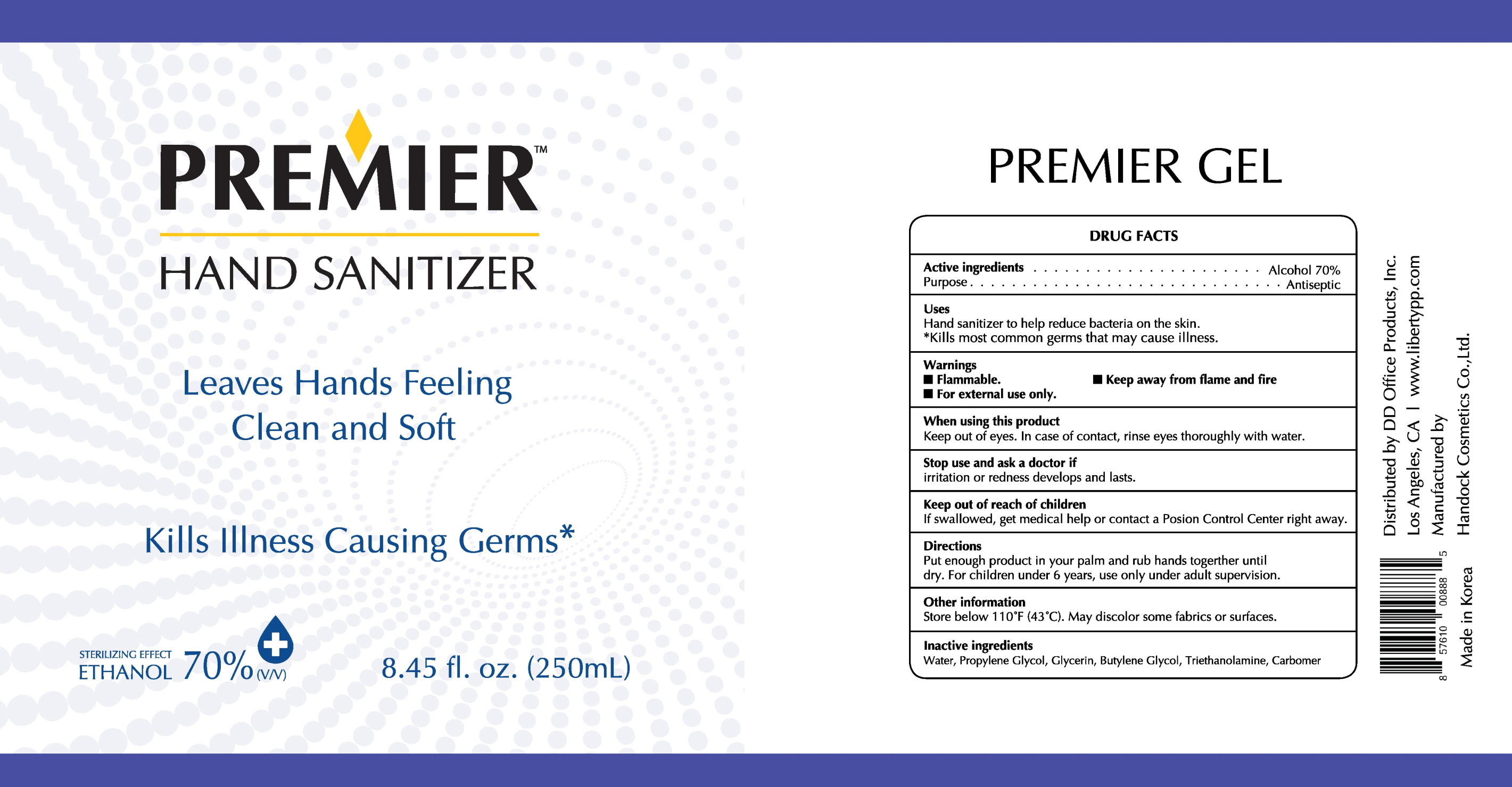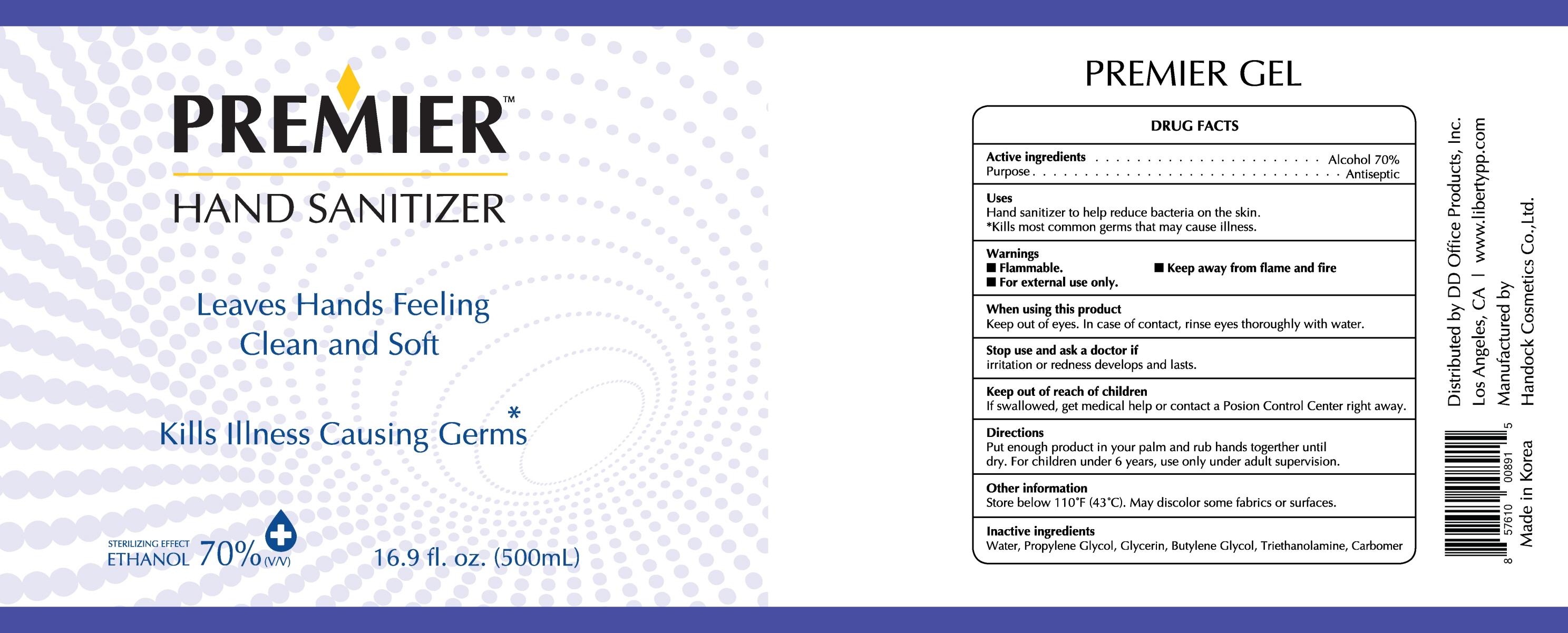 DRUG LABEL: PREMIER
NDC: 77081-020 | Form: GEL
Manufacturer: D D Office Products
Category: otc | Type: HUMAN OTC DRUG LABEL
Date: 20200529

ACTIVE INGREDIENTS: ALCOHOL 70 mL/100 mL
INACTIVE INGREDIENTS: Water; Propylene Glycol; Glycerin; TROLAMINE; CARBOMER HOMOPOLYMER, UNSPECIFIED TYPE

ACTIVE INGREDIENT

ALCOHOL 70%

INACTIVE INGREDIENTS

Water, Propylene Glycol, Glycerin, Butylene Glycol, Triethanolamine, Carbomer

PURPOSE

Antiseptic

WARNINGS

Flammable. Keep away from flame and fire. For external use only.

When using this product
Keep out of eyes. In case of contact, rinse eyes thoroughly with water.

Stop use and ask a doctor if
irritation or redness develops and lasts.

KEEP OUT OF REACH OF CHILDREN

If swallowed, get medical help or contact a Poison Control Center right away.

Uses

Hand sanitizer to help reduce bacteria on the skin.
*Kills most common germs that may cause illness.

Directions

Put enough product in your palm and rub hands together until dry.
For children under 6 years, use only under adult supervision.

Other information

Store below 110°F (43°C)
May discolor some fabrics or surfaces